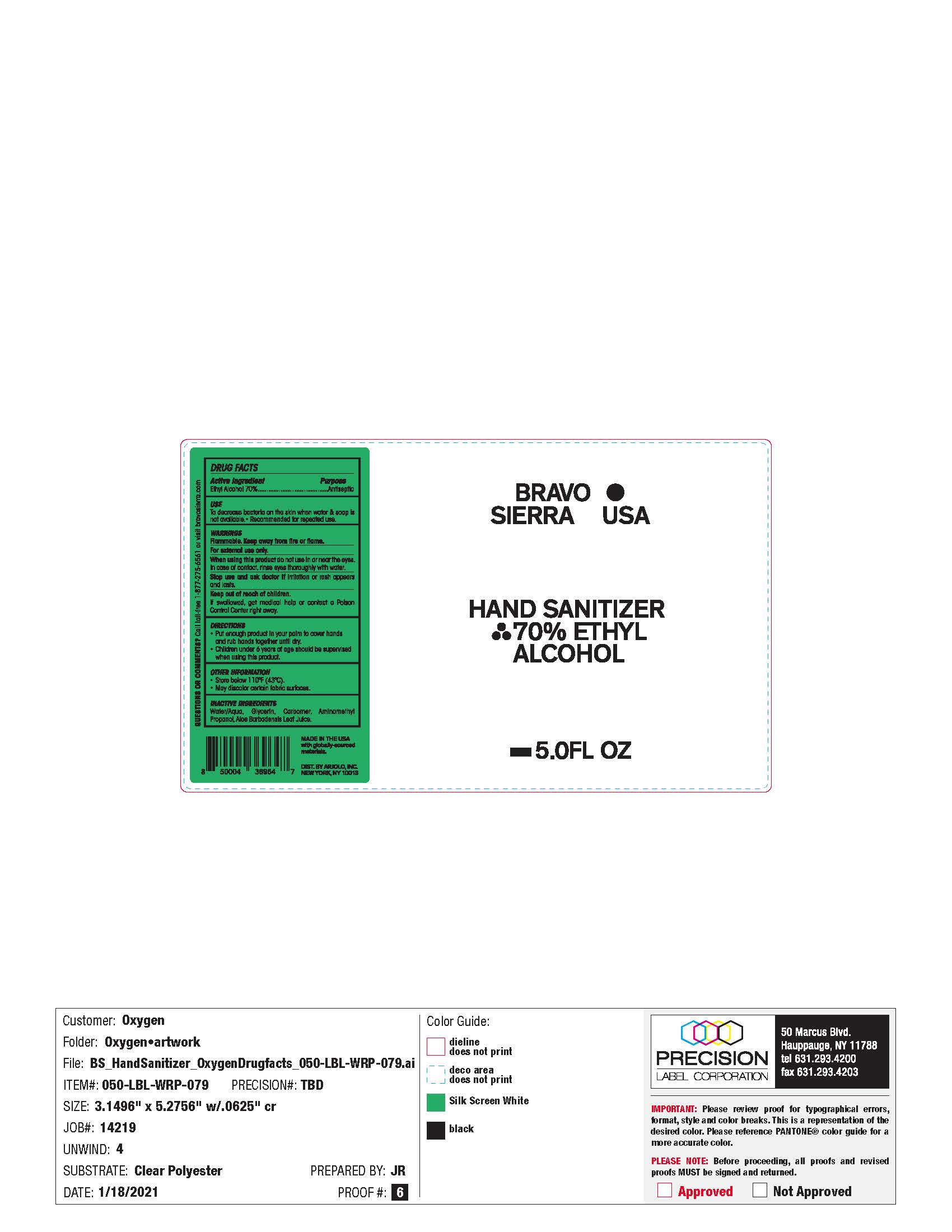 DRUG LABEL: Hand Sanitizer
NDC: 61354-015 | Form: GEL
Manufacturer: OXYGEN DEVELOPMENT, LLC
Category: otc | Type: HUMAN OTC DRUG LABEL
Date: 20210721

ACTIVE INGREDIENTS: ALCOHOL 70.473 mL/100 mL
INACTIVE INGREDIENTS: GLYCERIN 1.496 mL/100 mL; CARBOMER 940 0.5 mL/100 mL; WATER 27.445 mL/100 mL

BSHS-00-0001 - HAND SANITIZER 5 OZ

Active Ingredient(s)

Alcohol 70% . Purpose: Antiseptic

Purpose

Antiseptic, Hand Sanitizer

Use

Hand Sanitizer to help reduce bacteria on the skin.

Warnings

Flammable. Keep away from heat or flame.For external use only.

When using this product do not use in or near the eyes. In case of contact, rinse eyes throughly with water.

Stop Use

Stop use and ask a doctor if irritation or rash appears and lasts.

Keep out of reach of children. If swallowed, get medical help or contact a or contact a Poison Control Center right away.

Directions

- Place enough product in your palm to cover hands and rub hands together until dry.
- Children under 6 years of age should be supervised when using this product.

Other information

- Store below 110F(43C).
- May discolor certain fabric surfaces.

Inactive ingredients

Water/Aqua, Glycerin, Carbomer, Aminomenthyl Propanol, Aloe Barbadensis Leaf Juice.

Use

To decrease bacteria on the skin when water &soap is not available. Recomended for repeated use